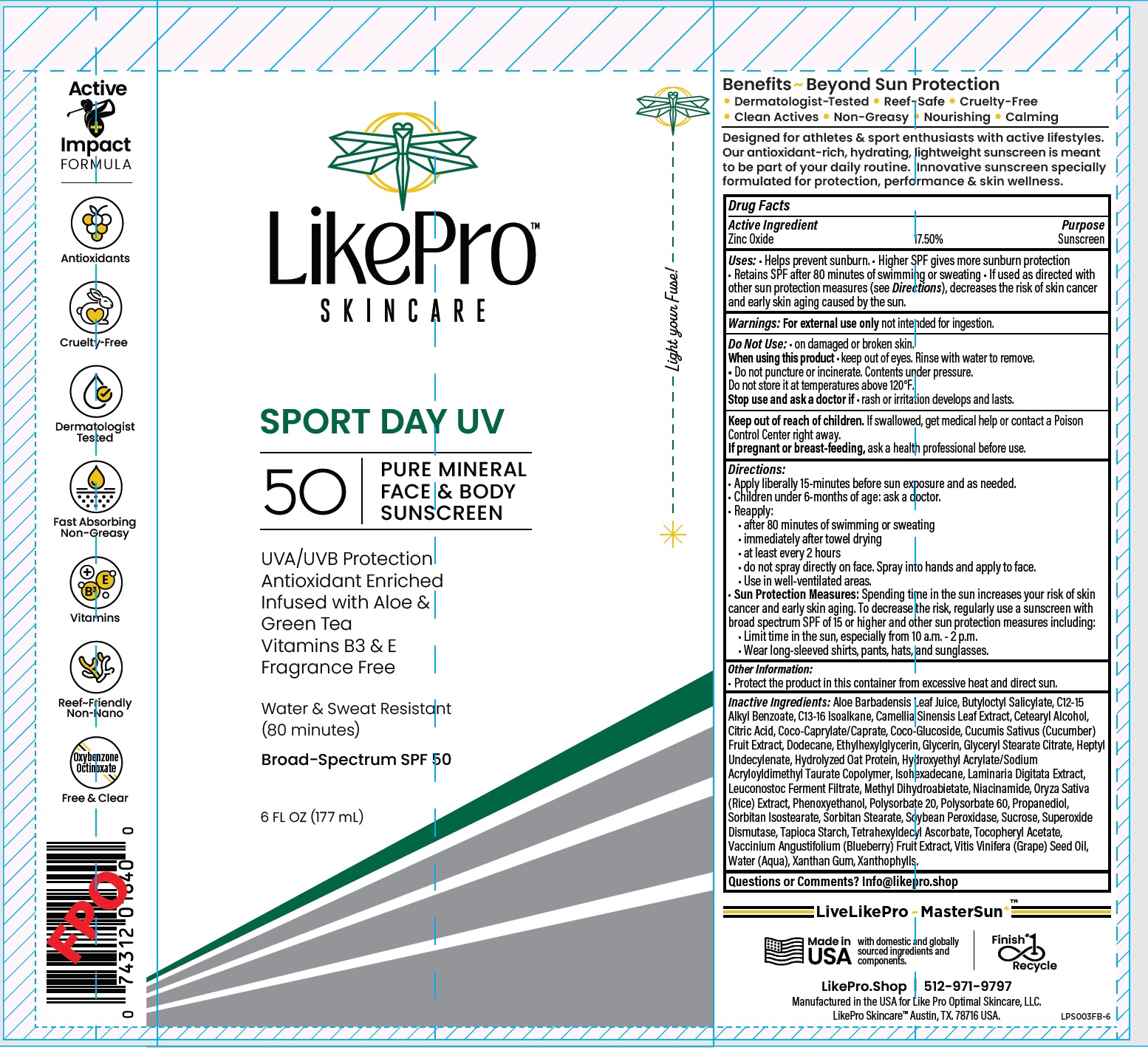 DRUG LABEL: LikePro Skincare Sport Day UV Face and Body Sunscreen SPF 50
NDC: 85750-612 | Form: LIQUID
Manufacturer: LIKE PRO OPTIMAL SKINCARE LLC
Category: otc | Type: HUMAN OTC DRUG LABEL
Date: 20250603

ACTIVE INGREDIENTS: ZINC OXIDE 175 mg/1 mL
INACTIVE INGREDIENTS: ALOE VERA LEAF JUICE; BUTYLOCTYL SALICYLATE; ALKYL (C12-15) BENZOATE; C13-16 ISOPARAFFIN; GREEN TEA LEAF; CAPRYLYL GLYCOL; CITRIC ACID MONOHYDRATE; COCOYL CAPRYLOCAPRATE; COCO-GLUCOSIDE; CUCUMBER; DODECANE; ETHYLHEXYLGLYCERIN; GLYCERIN; GLYCERYL STEARATE CITRATE; HEPTYL UNDECYLENATE; ISOHEXADECANE; LAMINARIA DIGITATA; METHYL DIHYDROABIETATE; NIACINAMIDE; RICE GERM; PHENOXYETHANOL; POLYSORBATE 20; POLYSORBATE 60; PROPANEDIOL; SORBITAN ISOSTEARATE; SORBITAN STEARATE; SUCROSE; SUPEROXIDE DISMUTASE; TAPIOCA STARCH; TETRAHEXYLDECYL ASCORBATE; .ALPHA.-TOCOPHEROL ACETATE; LOWBUSH BLUEBERRY; GRAPE SEED OIL; WATER; XANTHAN GUM

LikePro Skincare Sport Day UV Face and Body Sunscreen SPF 50

Active Ingredient

Zinc Oxide 17.50%

Purpose

Sunscreen

Uses:

- Helps prevent sunburn.
- Higher SPF gives more sunburn protection
- Retains SPF after 80 minutes of swimming or sweating
- If used as directed with other sun protection measures (see Directions), decreases the risk of skin cancer and early skin aging caused by the sun.

Warnings:

For external use only not intended for ingestion.

Do Not Use:

- on damaged or broken skin.

When using this product

- keep out of eyes. Rinse with water to remove.
- Do not puncture or incinerate. Contents under pressure.
  Do not store it at temperatures above 120°F.

Stop use and ask a doctor if

- rash or irritation develops and lasts.

Keep out of reach of children.

If swallowed, get medical help or contact a Poison Control Center right away.

If pregnant or breast-feeding,

ask a health professional before use.

Directions:

- Apply liberally 15-minutes before sun exposure and as needed.
- Children under 6-months of age: ask a doctor.
- Reapply:
- after 80 minutes of swimming or sweating
- immediately after towel drying
- at least every 2 hours
- Sun Protection Measures:Spending time in the sun increases your risk of skin cancer and early skin aging. To decrease the risk, regularly use a sunscreen with broad spectrum SPF of 15 or higher and other sun protection measures including:
- Limit time in the sun, especially from 10 a.m. - 2 p.m.
- Wear long-sleeved shirts, pants, hats, and sunglasses.

Other Information:

- Protect the product in this container from excessive heat and direct sun.

Inactive Ingredients:

Aloe Barbadensis Leaf Juice, Butyloctyl Salicylate, C12-15 Alkyl Benzoate, C13-16 Isoalkane, Camellia Sinensis Leaf Extract, Cetearyl Alcohol, Citric Acid, Coco-Caprylate/Caprate, Coco-Glucoside, Cucumis Sativus (Cucumber) Fruit Extract, Dodecane, Ethylhexylglycerin, Glycerin, Glyceryl Stearate Citrate, Heptyl Undecylenate, Hydrolyzed Oat Protein, Hydroxyethyl Acrylate/Sodium Acryloyldimethyl Taurate Copolymer, Isohexadecane, Laminaria Digitata Extract, Leuconostoc Ferment Filtrate, Methyl Dihydroabietate, Niacinamide, Oryza Sativa (Rice) Extract, Phenoxyethanol, Polysorbate 20, Polysorbate 60, Propanediol, Sorbitan Isostearate, Sorbitan Stearate, Soybean Peroxidase, Sucrose, Superoxide Dismutase, Tapioca Starch, Tetrahexyldecyl Ascorbate, Tocopheryl Acetate, Vaccinium Angustifolium (Blueberry) Fruit Extract, Vitis Vinifera (Grape) Seed Oil, Water (Aqua), Xanthan Gum, Xanthophylls.

Questions or Comments?

Info@likepro.shop